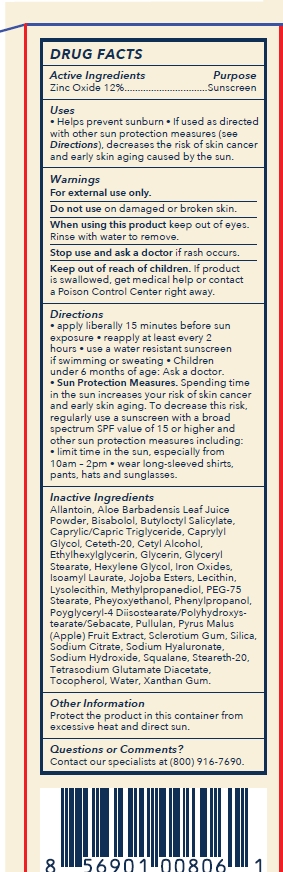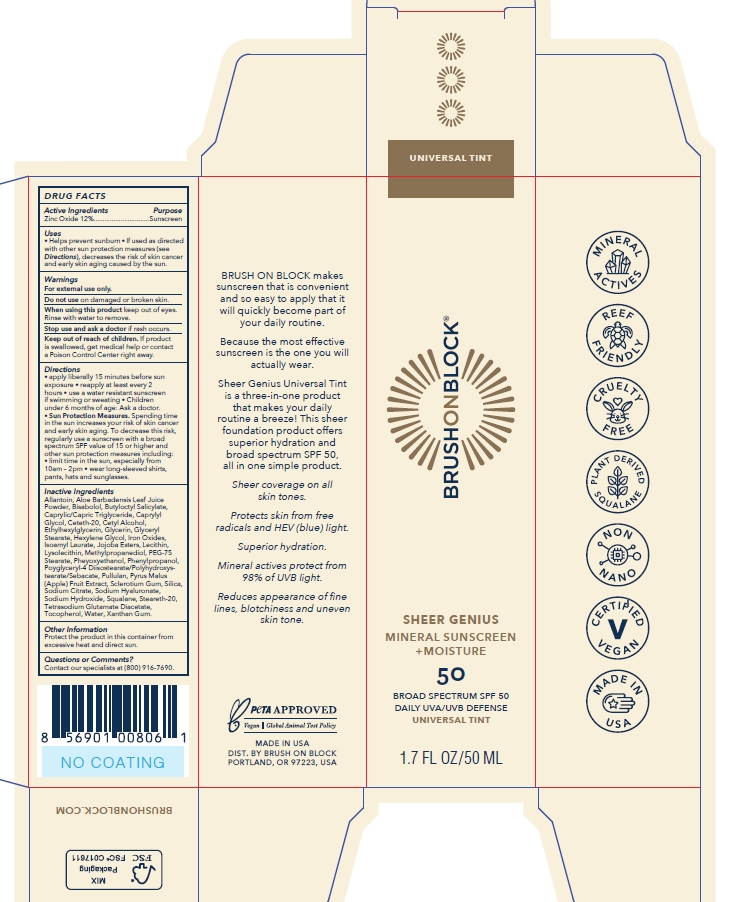 DRUG LABEL: Brush On Block Sheer Genius SPF 50 Mineral Moisture Universal Tint
NDC: 58274-019 | Form: LOTION
Manufacturer: SPF Ventures, LLC
Category: otc | Type: HUMAN OTC DRUG LABEL
Date: 20240308

ACTIVE INGREDIENTS: ZINC OXIDE 12 g/100 mL
INACTIVE INGREDIENTS: TOCOPHEROL; TETRASODIUM GLUTAMATE DIACETATE; PULLULAN; SILICON DIOXIDE; HYALURONATE SODIUM; SODIUM HYDROXIDE; BUTYLOCTYL SALICYLATE; CETETH-20; JOJOBA OIL, RANDOMIZED; GLYCERIN; FERRIC OXIDE RED; ISOAMYL LAURATE; LECITHIN, SOYBEAN; MEDIUM-CHAIN TRIGLYCERIDES; HEXYLENE GLYCOL; POLYGLYCERYL-2 DIPOLYHYDROXYSTEARATE; BETASIZOFIRAN; ALLANTOIN; LEVOMENOL; CAPRYLYL GLYCOL; CETYL ALCOHOL; ETHYLHEXYLGLYCERIN; GLYCERYL MONOSTEARATE; LYSOPHOSPHATIDYLCHOLINE, SOYBEAN; METHYLPROPANEDIOL; PEG-75 STEARATE; PHENOXYETHANOL; PHENYLPROPANOL; APPLE; SODIUM CITRATE; SQUALANE; STEARETH-20; WATER; XANTHAN GUM; ALOE VERA LEAF

Brush On Block Sheer Genius SPF 50 Mineral + Moisture Universal Tint

Active ingredient

Zinc Oxide 12%

Purpose

Sunscreen

Uses

- Helps prevent sunburn
- If used as directed with other sun protection measures (see Directions), decreases the risk of skin cancer and early skin aging caused by the sun.

Warnings

For external use only

Do not use on damaged or broken skin

When using this product keep out of eyes. Rinse with water to remove.

Stop use and ask a doctor if rash occurs.

Keep out of reach of children

If product is swallowed, get medical help or contact a Poison Control Center right away.

Directions

- apply liberally 15 minutes before sun exposure.
- reapply at least every 2 hours
- use a water resistant sunscreen if swimming or sweating
- Children under 6 months of age: Ask a doctor.
- Sunprotection Measures. Spending time in the sun increases your risk of skin cancer and early skin aging. To decrease this risk, regularly use a sunscreen with a broad spectrum SPF value of 15 or higher and other sun protection measures including:
- limit time in the sun, especially from 10am-2pm
- wear long-sleeved shirts, pants, hats and sunglasses.

Inactive Ingredients

Allantoin

Aloe Barbadensis Leaf Juice Powder

Bisabolol

Butyloctyl Salicylate

Caprylic/Capric Triglyceride

Caprylyl Glycol

Ceteth-20

Cetyl Alcohol

Ethylhexylglycerin

Glycerin

Glyceryl Stearate

Hexylene Glycol

Iron Oxides

Isoamyl Laurate

Jojoba Esters

Lecithin

Lysolecithin

Methylpropanediol

PEG-75 Stearate

Phenoxyethanol

Phenylpropanol

Polyglyceryl-2 Diplolyhydroxystearate

Pullulan

Pyrus Malus (Apple) Fruit Extract

Sclerotium Gum

Silica

Sodium Citrate

Sodium Hyaluronate

Sodium Hydroxide

Squalane

Steareth-20

Tetrasodium Glutamate Diacetate

Tocopherol

Water

Xanthan Gum

Other information

Protect the product in this container from excessive heat and direct sun.